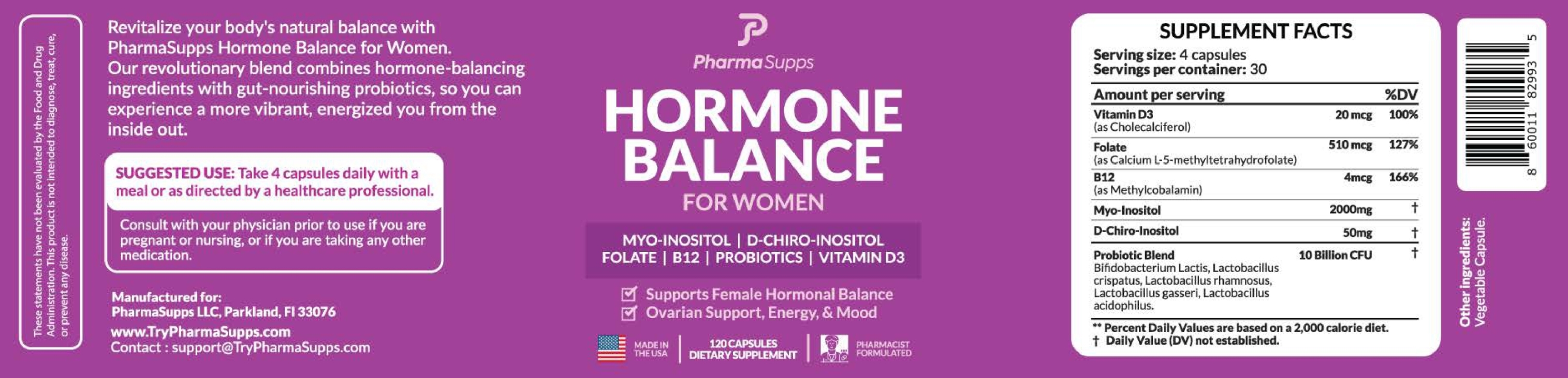 DRUG LABEL: Hormon Balance
NDC: 87260-001 | Form: CAPSULE
Manufacturer: PharmaSupps LLP
Category: other | Type: Dietary Supplement
Date: 20251208

ACTIVE INGREDIENTS: INOSITOL 2000 mg/1 1; CHIRO-INOSITOL, (+)- 50 mg/1 1; LEVOMEFOLATE CALCIUM 510 ug/1 1; CYANOCOBALAMIN 4 ug/1 1; CHOLECALCIFEROL 20 ug/1 1

Hormon Balance for Women

STATEMENT OF IDENTITY

Hormon Balance Capsules for Women

- Supports Female Hormonal Balance
- Ovarian Support, Energy and Mood